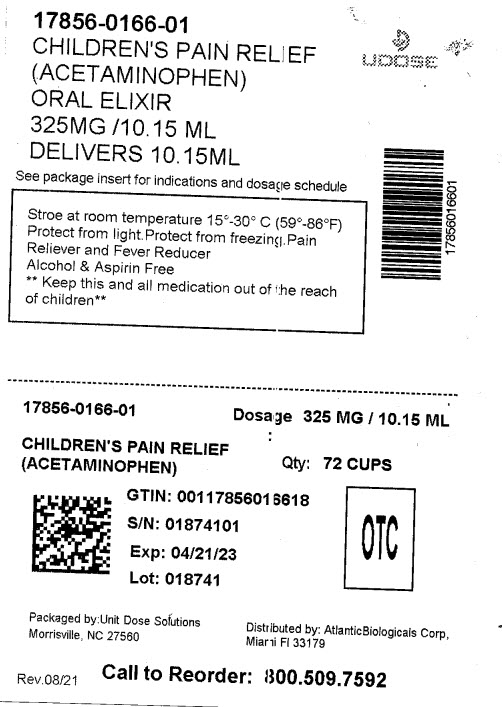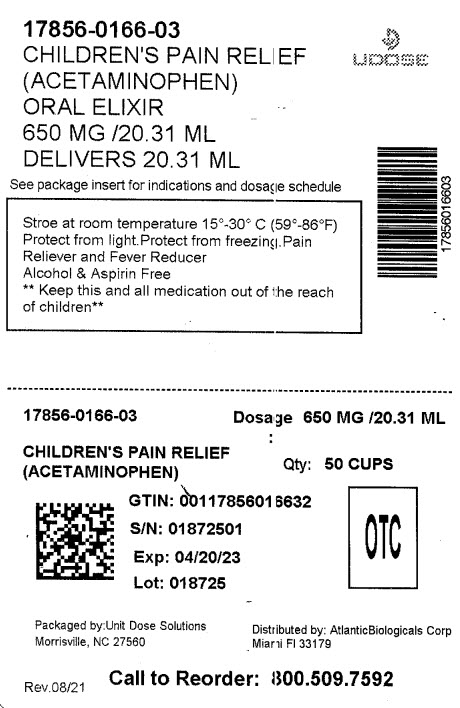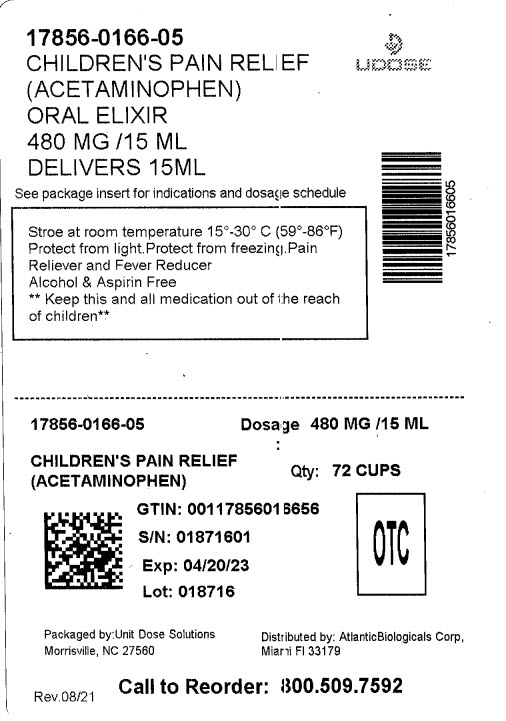 DRUG LABEL: ACETAMINOPHEN
NDC: 17856-0166 | Form: ELIXIR
Manufacturer: ATLANTIC BIOLOGICALS CORP
Category: otc | Type: HUMAN OTC DRUG LABEL
Date: 20230313

ACTIVE INGREDIENTS: ACETAMINOPHEN 160 mg/5 mL
INACTIVE INGREDIENTS: CITRIC ACID MONOHYDRATE; FD&C RED NO. 40; GLYCERIN; POLYETHYLENE GLYCOL 400; WATER; SODIUM CITRATE; SACCHARIN SODIUM; SORBITOL; SODIUM BENZOATE

Acetaminophen Elxir
Bubble Gum Flavor

Active ingredient (in each 5 mL)

Acetaminophen 160 mg

Purpose

Pain Reliever/Fever Reducer

Uses

trmporarily:

- reduces fever
- relieves minor aches and pains due to:
- the common cold
- flu
- headache
- sore throat
- toothache

Warnings

Liver warning

This product contains acetaminophen.

Severe liver damage may occur if your child takes:

- more than 5 doses in 24 hours, which is the maximum daily amount
- with other drugs containing acetaminophen.

Allergy alert:

Acetaminophen may cause severe skin reactions. Symptoms may include:

- skin reddening
- blisters
- rash

If a skin reaction occurs, stop use and seek medical help right away.

Sore throat warning:

If sore throat is severe, persists for more than 2 days, is accompanied or followed by fever, headache, rash, nausea, or vomiting, consult a doctor promptly.

Do not use

- with any other drug containing acetaminophen (prescription or non-prescription). If you are not sure whether a drug contains acetaminophen, ask a doctor or pharmacist.
- if your child is allergic to acetaminophen or any of the inactive ingredients in this product

Ask a doctor before use if your child has

- liver disease

Ask a doctor or pharmacist before use if your child is taking the blood thinning drug warfarin

When using this product: Do not exceed recommended dose

Stop use and ask a doctor if:

- Pain gets worse or lasts more than 5 days
- fever gets worse or lasts more than 3 days
- new symptoms occur.
- redness or swelling is present.

These could be signs of a serious condition.

Keep out of reach of children.

Overdose Warning:

In case of overdose get medical help or contact a Poison Control Center (1-800-222-1222) right away. Quick medical
attention is critical even if you do not notice any signs or symptoms.

Directions

- this product does not contain directions or complete warnings for adult use
- shake well before using
- mL=milliliter
- find the right dose on chart below, if possible, use weight to dose; otherwise use age
- use only the enclosed dosing cup designed for use with this product.
- Do not use any other dosing device.
- if needed, repeat dose every 4 hours while symptoms last
- do not give more than 5 times in 24 hours
- do not give more than 5 days unless directed by doctor.

Weight (lbs.) | Age (years) | dosage-teaspoonful (tsp.)
under 24 | under 2 | ask a doctor
24 to 35 | 2 to 3 | 1 tsp or 5 mL
36 to 47 | 4 to 5 | 1 1/2 tsp or 7.5 mL
48 to 59 | 6 to 8 | 2 tsp or 10 mL
60 to 71 | 9 to 10 | 2 1/2 tsp or 12.5 mL
72 to 95 | 11 | 3 tsp or 15 mL

Other information

- Store at room temperature 15°-30° C (59°-86°F)
- Protect from Freezing.
- Protect from Light.

TAMPER EVIDENT: DO NOT USE IF BREAKAWAY BAND ON CAP IS BROKEN OR MISSING.

Inactive Ingredients:

bubble gum flavor, citric acid, glycerin, polyethylene glycol 400, purified water, sodium citrate, saccharin sodium, sorbitol solution & sodium benzoate.

Questions or Comments?

Call (877) 225-6999 Monday - Friday 9AM-5PM EST

DISTRIBUITED BY:

ATLANTIC BIOLOGICALS CORP.

MIAMI, FL 33179

* This product is not manufactured or distributed by McNeil Consumer Healthcare, owner of the registered trademark Tylenol Elixir